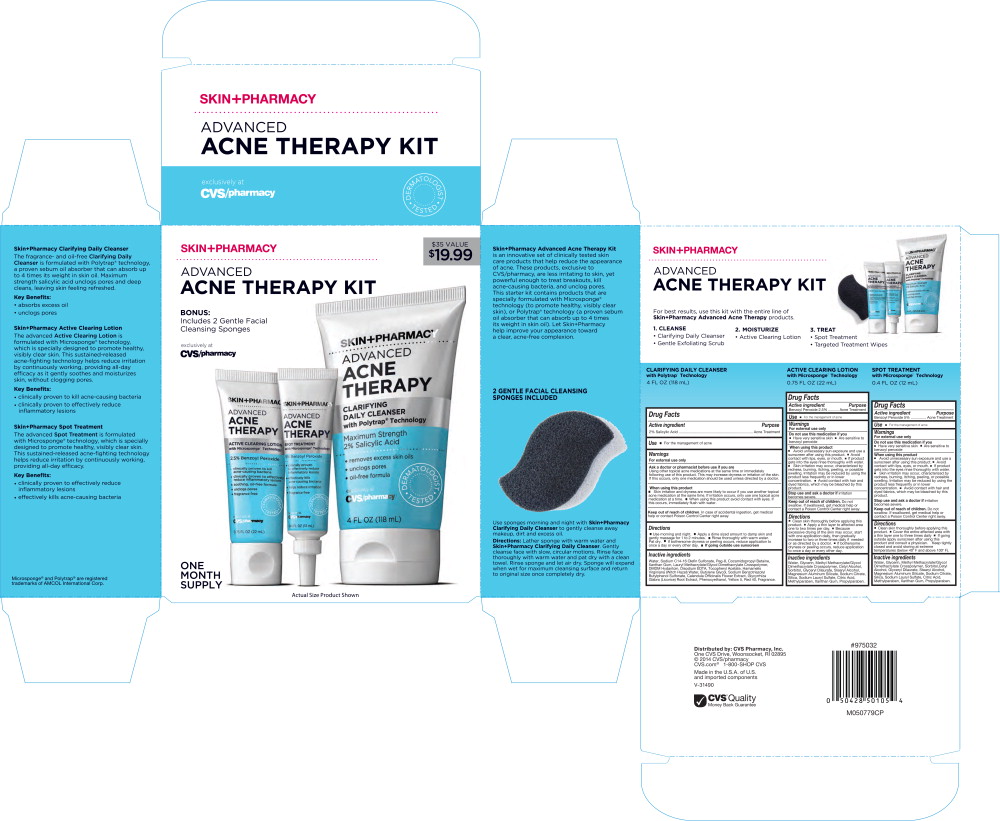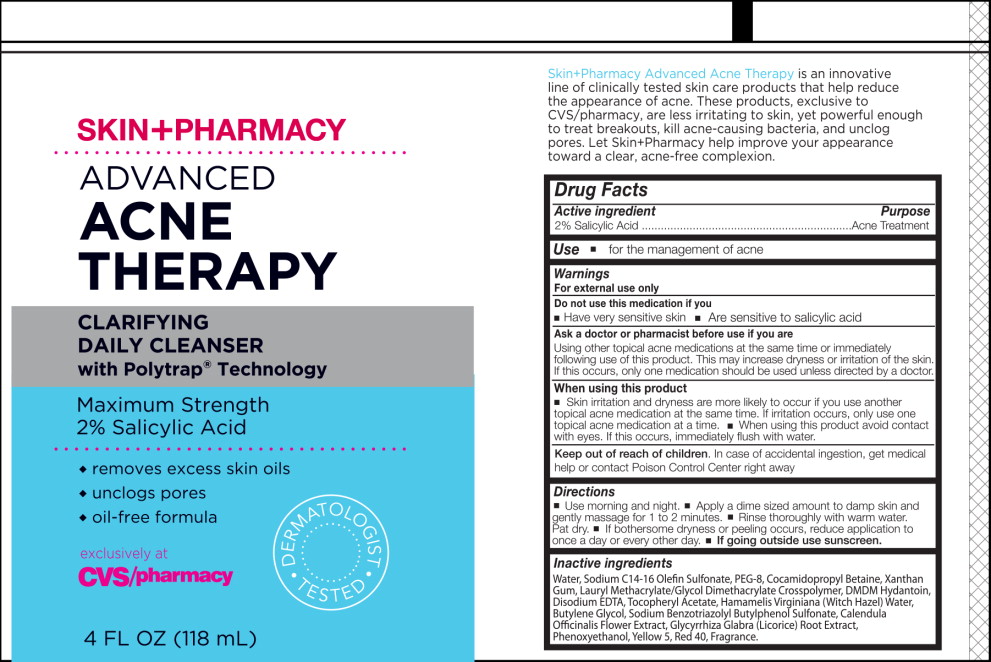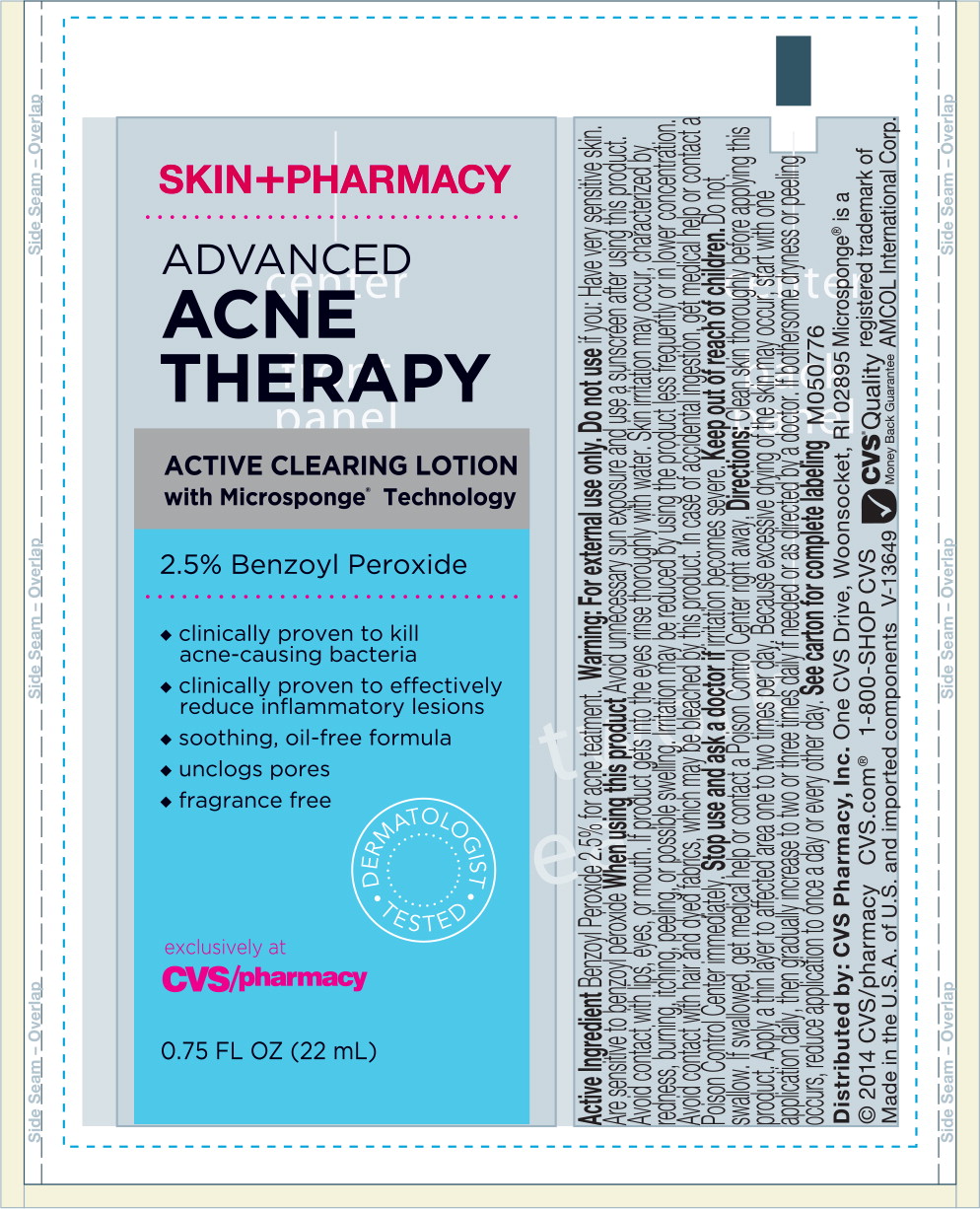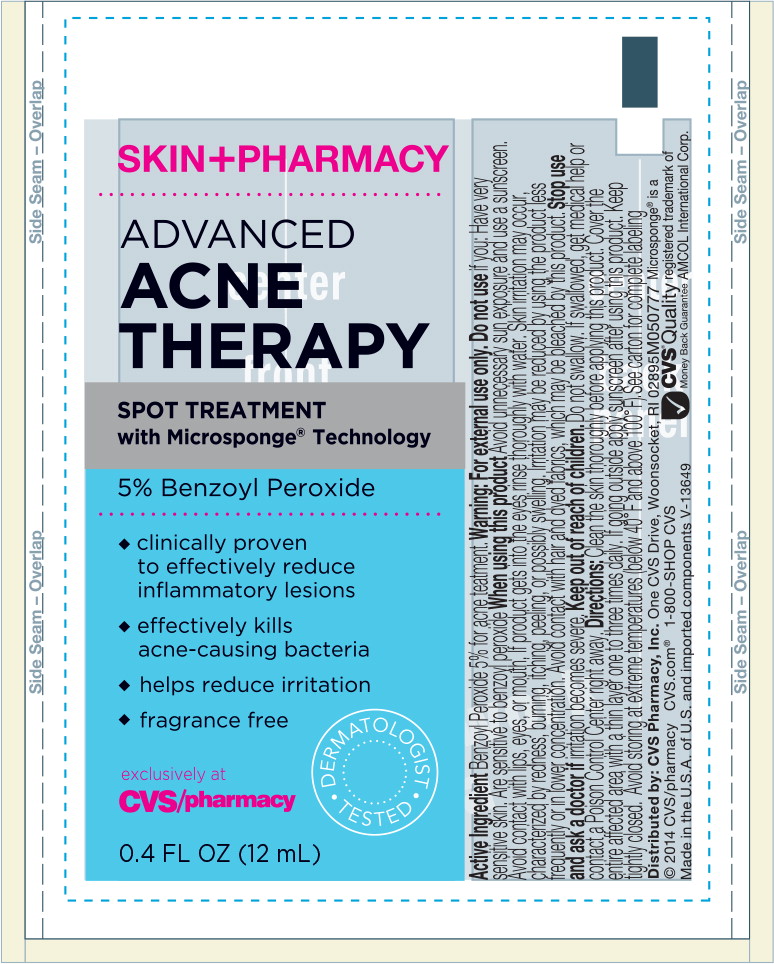 DRUG LABEL: Skin Pharmacy Advanced Acne Therapy Kit
NDC: 68634-067 | Form: KIT | Route: TOPICAL
Manufacturer: AMCOL Health & Beauty Solutions, Inc. DBA
Category: otc | Type: HUMAN OTC DRUG LABEL
Date: 20161011

ACTIVE INGREDIENTS: salicylic acid 20 g/2 mL; benzoyl peroxide 25 g/2 mL; benzoyl peroxide 50 g/2 mL
INACTIVE INGREDIENTS: Water; sodium C14-16 olefin sulfonate; polyethylene glycol 4000; cocamidopropyl betaine; Xanthan gum; DMDM Hydantoin; edetate disodium; .alpha.-tocopherol acetate, DL-; Hamamelis virginiana flower water; Butylene glycol; Calendula Officinalis flower; licorice; Phenoxyethanol; FD&C Yellow No. 5; FD&C red no. 40; Lauryl Methacrylate/Glycol Dimethacrylate Crosspolymer; water; glycerin; methyl methacrylate/glycol dimethacrylate crosspolymer; cetyl alcohol; sorbitol; glyceryl dilaurate; stearyl alcohol; magnesium aluminum silicate; sodium citrate; silicon dioxide; sodium lauryl sulfate; citric acid monohydrate; methylparaben; xanthan gum; propylparaben; water; glycerin; methyl methacrylate/glycol dimethacrylate crosspolymer; cetyl alcohol; sorbitol; glyceryl dilaurate; stearyl alcohol; magnesium aluminum silicate; sodium citrate; silicon dioxide; sodium lauryl sulfate; citric acid monohydrate; methylparaben; xanthan gum; propylparaben

Drug Facts

Active Ingredient

2% Salicylic Acid

Purpose

Acne Treatment

Use

- for the management of acne

Warnings

For external use only

Do not use this medication if you

- Have very sensitive skin
- Are sensitive to salicylic acid

Ask a doctor or pharmacist before use if you are

Using other topical acne medications at the same time or immediately following use of this product. This may increase dryness or irritation of the skin. If this occurs, only one medication should be used unless directed by a doctor.

When using this product

- Skin irritation and dryness are more likely to occur if you use another topical acne medication at the same time. If irritation occurs, only use one topical acne medication at a time.
- When using this product avoid contact with eyes. If this occurs, immediately flush with water.

Keep out of reach of children. In case of accidental ingestion, get medical help or contact Poison Control Center right away.

Directions

- Use morning and night.
- Apply a dime sized amount to damp skin and gently massage for 1 to 2 minutes.
- Rinse thoroughly with warm water.
- Pat dry.
- If bothersome dryness or peeling occurs, reduce application to once a day or every other day.
- If going outside use sunscreen.

Inactive ingredients

Water, Sodium C14-16 Olefin Sulfonate, Peg-8, Cocamidopropyl Betaine, Xanthan Gum, Lauryl Methacrylate/Glycol Dimethacrylate Crosspolymer, DMDM Hydantoin, Disodium EDTA, Tocopheryl Acetate, Hamamelis Virginiana (Witch Hazel) Water, Butylene Glycol, Sodium Benzotriazolyl Butylphenol Sulfonate, Calendula Officinalis Flower Extract, Glycyrrhiza Glabra (Licorice) Root Extract, Phenoxyethanol, Yellow 5, Red 40, Fragrance.

M050775

Principal Display Panel - Skin+Pharmacy Advanced Acne Therapy Kit Carton Label

SKIN+PHARMACY

ADVANCED
ACNE THERAPY KIT

DERMATOLOGIST TESTED

BONUS:

Includes 2 Gentle Facial

Cleansing Sponges

exclusively at
CVS/pharmacy

$35 VALUE

$19.99

ONE MONTH SUPPLY

Principal Display Panel - Skin+Pharmacy Advanced Acne Therapy Kit Label

SKIN+PHARMACY

ADVANCED
ACNE
THERAPY

CLARIFYING
DAILY CLEANSER
with Polytrap® Technology

Maximum Strength

2% Salicylic Acid

- removes excess skin oils
- unclogs pores
- oil-free formula

DERMATOLOGIST TESTED

exclusively at
CVS/pharmacy

4 FL OZ (118 mL)

Principal Display Panel - Skin+Pharmacy Advanced Acne Therapy Kit Label

SKIN+PHARMACY

ADVANCED
ACNE
THERAPY

ACTIVE CLEARING LOTION
with Microsponge® Technology

2.5% Benzoyl Peroxide

- clinically proven to kill acne-causing bacteria
- clinically proven to effectively reduce inflammatory lesions
- soothing, oil-free formula
- unclogs pores
- fragrance free

DERMATOLOGIST TESTED

exclusively at
CVS/pharmacy

0.75 FL OZ (22 mL)

Principal Display Panel - Skin+Pharmacy Advanced Acne Therapy Kit Label

SKIN+PHARMACY

ADVANCED
ACNE
THERAPY

SPOT TREATMENT
with Microsponge® Technology

5% Benzoyl Peroxide

- clinically proven to effectively reduce inflammatory lesions
- effectively kills acne-causing bacteria
- helps reduce irritation
- fragrance free

DERMATOLOGIST TESTED

exclusively at
CVS/pharmacy

0.4 FL OZ (12 mL)